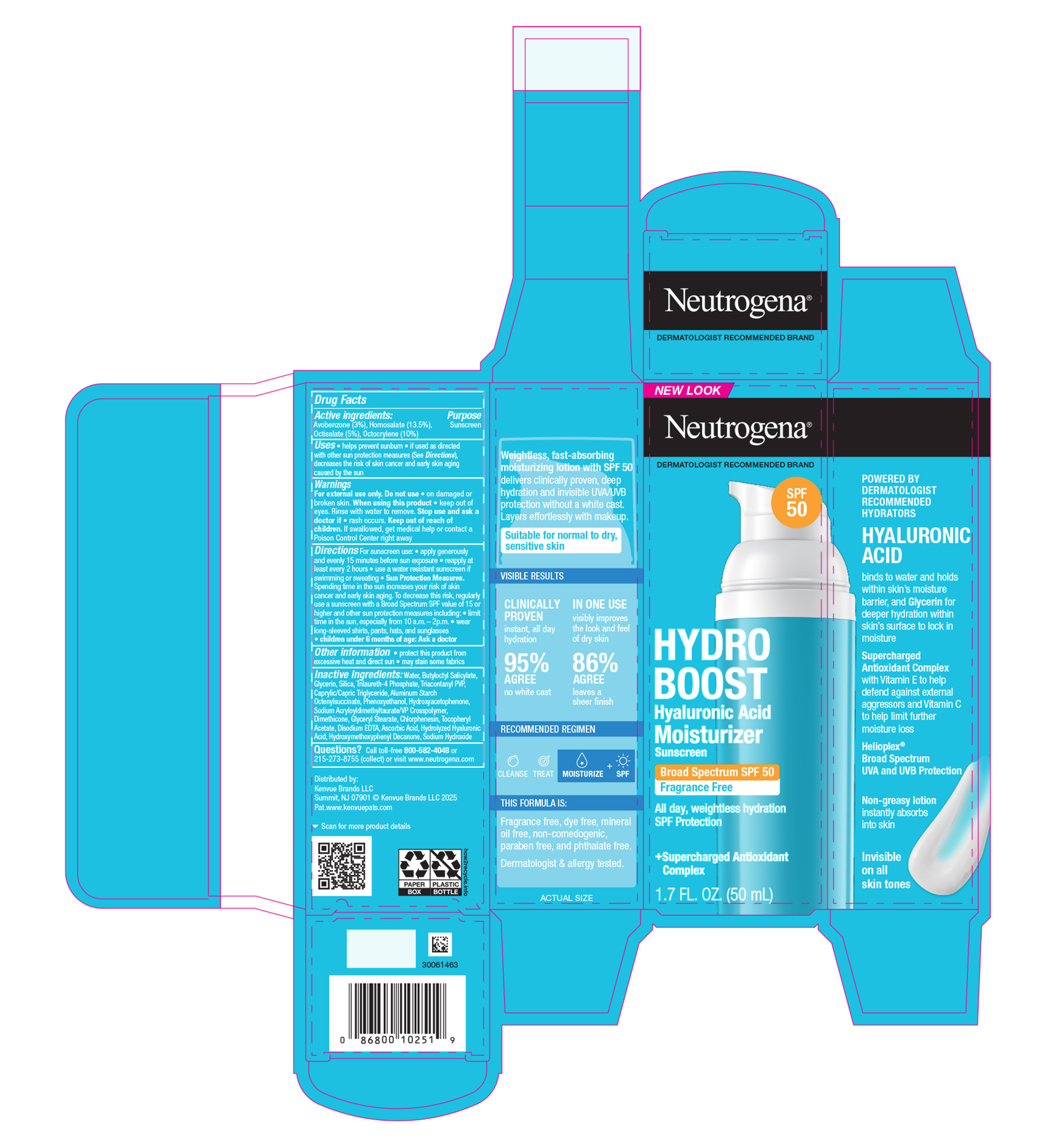 DRUG LABEL: Neutrogena Hydro Boost Hyaluronic Acid Moisturizer Broad Spectrum SPF 50
NDC: 69968-0932 | Form: LOTION
Manufacturer: Kenvue Brands LLC
Category: otc | Type: HUMAN OTC DRUG LABEL
Date: 20250828

ACTIVE INGREDIENTS: OCTISALATE 50 mg/1 mL; AVOBENZONE 30 mg/1 mL; HOMOSALATE 135 mg/1 mL; OCTOCRYLENE 100 mg/1 mL
INACTIVE INGREDIENTS: PHENOXYETHANOL; GLYCERYL STEARATE; EDETATE DISODIUM; GLYCERIN; TRIACONTANYL PVP; DIMETHICONE; SODIUM HYDROXIDE; WATER; BUTYLOCTYL SALICYLATE; SILICA; TRILAURETH-4 PHOSPHATE; HYDROXYACETOPHENONE; ALUMINUM STARCH OCTENYLSUCCINATE; HYDROXYMETHOXYPHENYL DECANONE; .ALPHA.-TOCOPHEROL ACETATE; ASCORBIC ACID; CAPRYLIC/CAPRIC TRIGLYCERIDE; CHLORPHENESIN

Neutrogena® HYDRO BOOST Hyaluronic Acid Moisturizer Broad Spectrum SPF 50

Drug Facts

ACTIVE INGREDIENT

Avobenzone 3%
Homosalate 13.5%
Octisalate 5%
Octocrylene 10%.

Active ingredients | Purpose
Avobenzone 3% | Sunscreen
Homosalate 13.5% | Sunscreen
Octisalate 5% | Sunscreen
Octocrylene 10%. | Sunscreen

Uses

- helps prevent sunburn
- if used as directed with other sun protection measures (see Directions), decreases the risk of skin cancer and early skin aging caused by the sun

Warnings

For external use only.

Do not use on damaged or broken skin.

When using this product keep out of eyes. Rinse with water to remove.

Stop use and ask a doctor if rash occurs.

Keep out of reach of children. If swallowed, get medical help or contact a Poison Control Center right away

Directions

For sunscreen use:

- apply generously and evenly 15 minutes before sun exposure
- reapply at least every 2 hours
- use a water resistant sunscreen if swimming or sweating
- Sun Protection Measures: Spending time in the sun increases your risk of skin cancer and early skin aging. To decrease this risk, regularly use a sunscreen with a Broad Spectrum SPF value of 15 or higher and other sun protection measures including:
  - limit time in the sun, especially from 10 a.m.-2 p.m.
  - wear long-sleeved shirts, pants, hats, and sunglasses
- children under 6 months of age: Ask a doctor.

Other information

- protect this product from excessive heat and direct sun
- may stain some fabrics

Inactive ingredients

Water, Butyloctyl Salicylate, Glycerin, Silica, Trilaureth-4 Phosphate, Triacontanyl PVP, Caprylic/Capric Triglyceride, Aluminum Starch Octenylsuccinate, Phenoxyethanol, Hydroxyacetophenone, Sodium Acryloyldimethyltaurate/VP Crosspolymer,

Dimethicone, Glyceryl Stearate, Chlorphenesin, Tocopheryl Acetate, Disodium EDTA, Ascorbic Acid, Hydrolyzed Hyaluronic Acid, Hydroxymethoxyphenyl Decanone, Sodium Hydroxide

Questions?

Call toll-free 800-582-4048 or 215-273-8755 (collect) or visit www.neutrogena.com

Distributed by:
Kenvue Brands LLC
Summit, NJ 07901

PRINCIPAL DISPLAY PANEL - 50 mL Bottle Carton

New Look

Neutrogena®

DERMATOLOGIST RECOMMENDED BRAND

SPF

50

HYDRO

BOOST

Hyaluronic Acid

Moisturizer

Sunscreen

Broad Spectrum SPF 50

Fragrance Free

All day, weightless hydration

SPF Protection

+Supercharged Antioxidant

Complex

1.7 FL OZ (50mL)